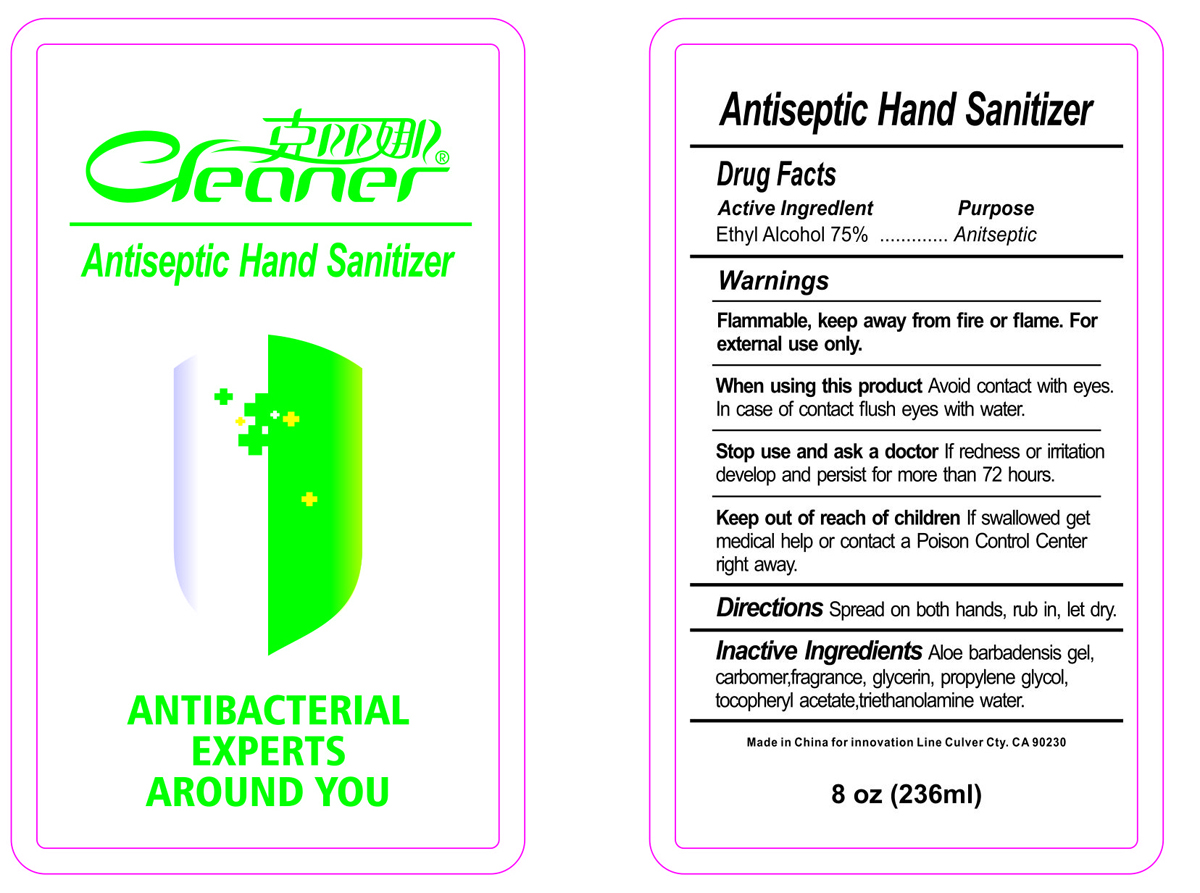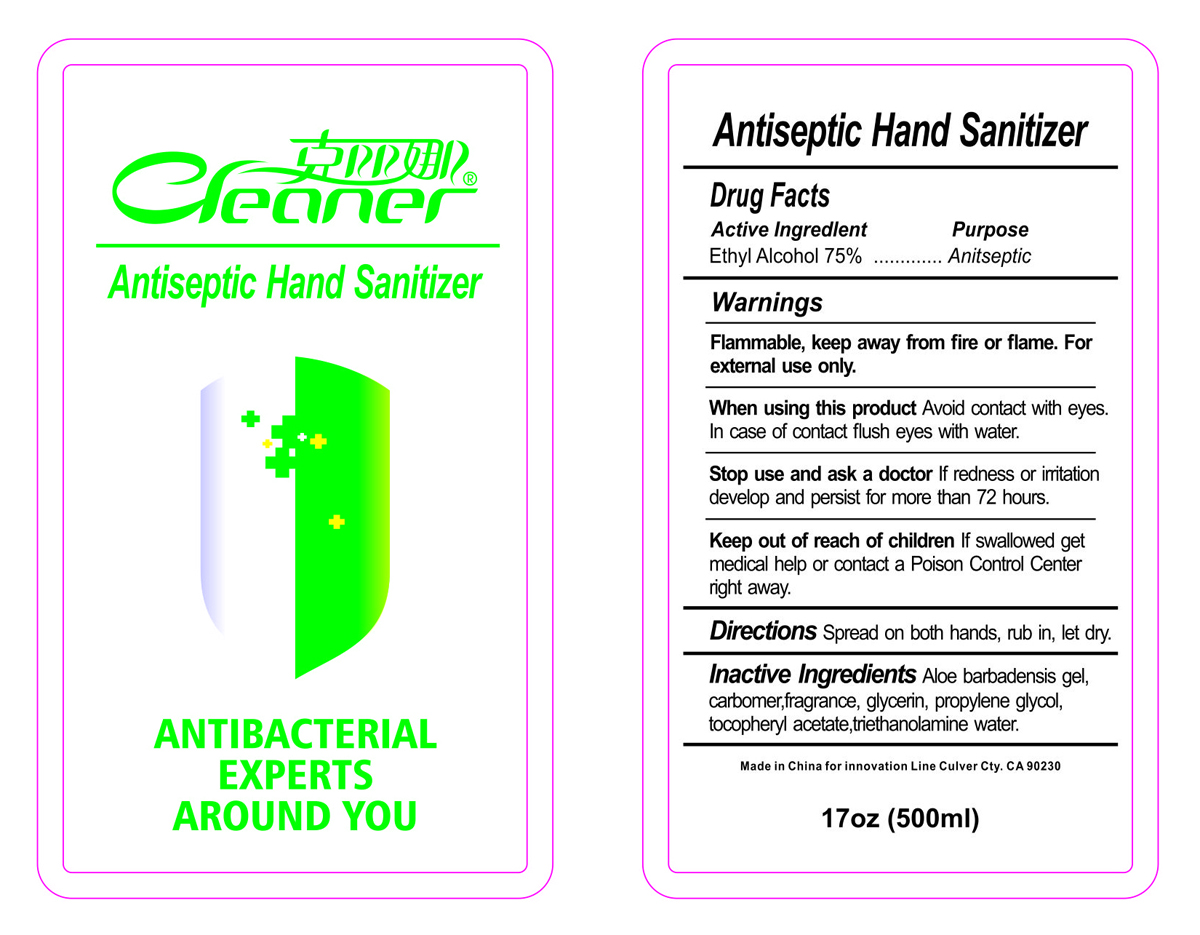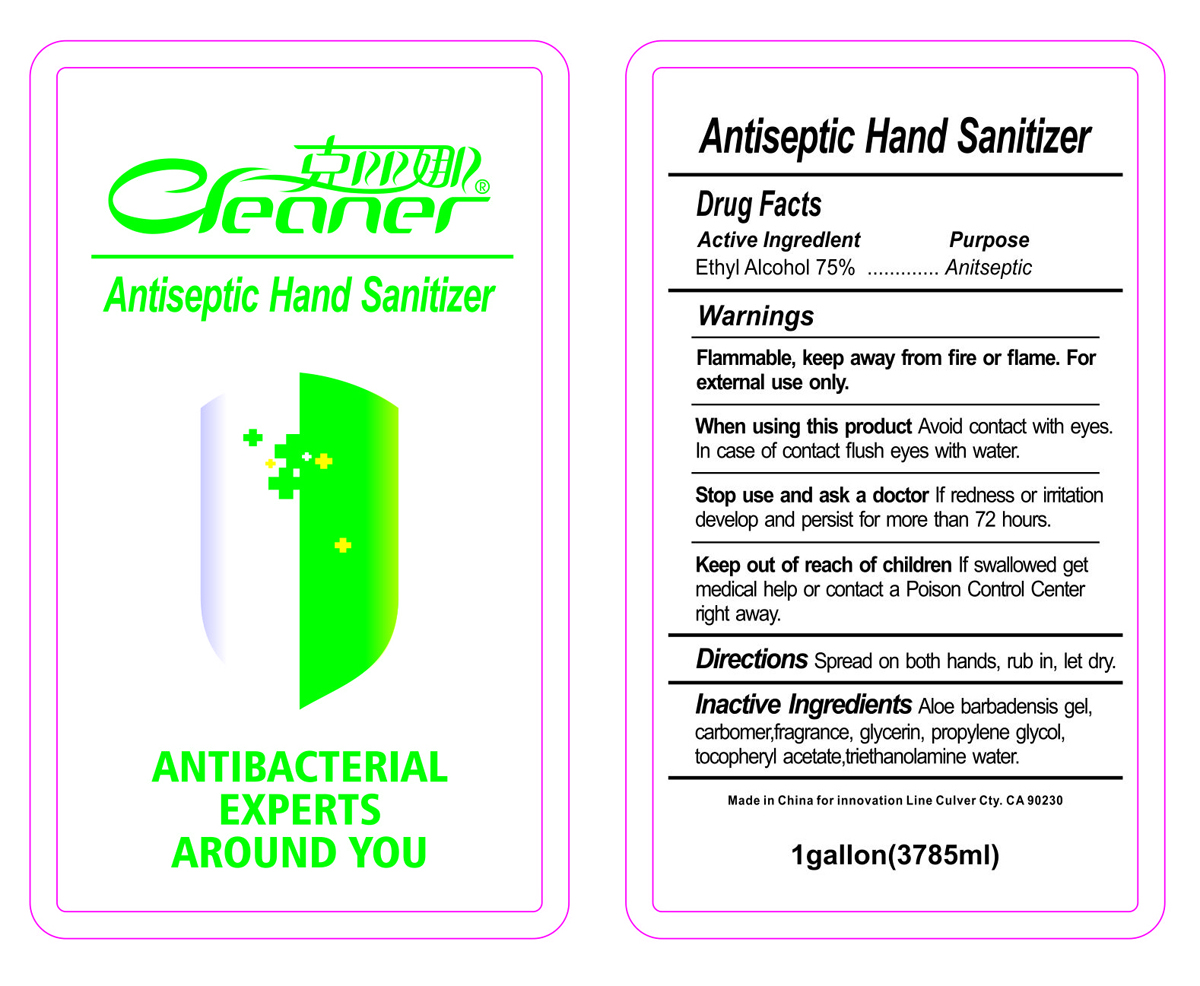 DRUG LABEL: Hand Sanitizer
NDC: 75729-001 | Form: GEL
Manufacturer: Ningbo Yaohu Bio-technology Co.ltd
Category: otc | Type: HUMAN OTC DRUG LABEL
Date: 20200509

ACTIVE INGREDIENTS: ALCOHOL 75 mL/100 mL
INACTIVE INGREDIENTS: CARBOMER HOMOPOLYMER, UNSPECIFIED TYPE; GLYCERIN; ALPHA-TOCOPHEROL ACETATE; WATER; TROLAMINE; PROPYLENE GLYCOL; ALOE VERA LEAF

Hand sanitizer

Active Ingredient(s)

Alcohol 75% v/v. Purpose: Antiseptic

Purpose

Antiseptic, Hand Sanitizer

Use

Antiseptic Hand Sanitizer

Warnings

Flammable. Keep away from heat or flame. For external use only.

WHEN USING

Avoid contact with eyes. In case of contact flush eyes with water.

Stop use and ask a doctor if redness or irritation develop and persist for more than 72 hours.

Keep out of reach of children. If swallowed, get medical help or contact a Poison Control Center right away.

Directions

Spread on both hands, rub it, let dry.

Inactive ingredients

Aloe barbadensis gel, carbomer, fragrance, glycerin, propylene glycol, tocopheryl acetate, triethanolamine, water

Package Label - Principal Display Panel

236 mL NDC: 75729-001-01

500 mL NDC: 75729-001-02

3785 mL NDC: 75729-001-03